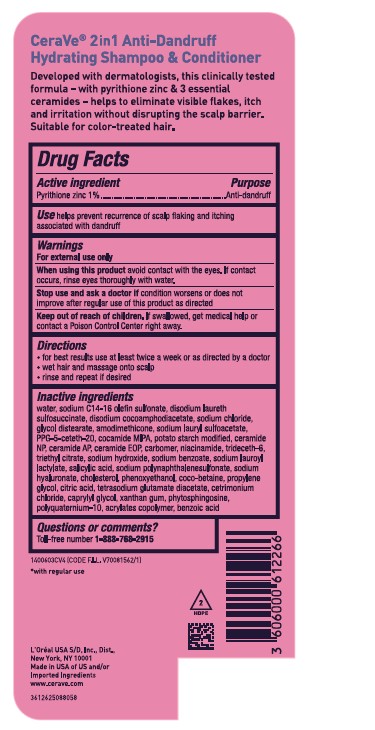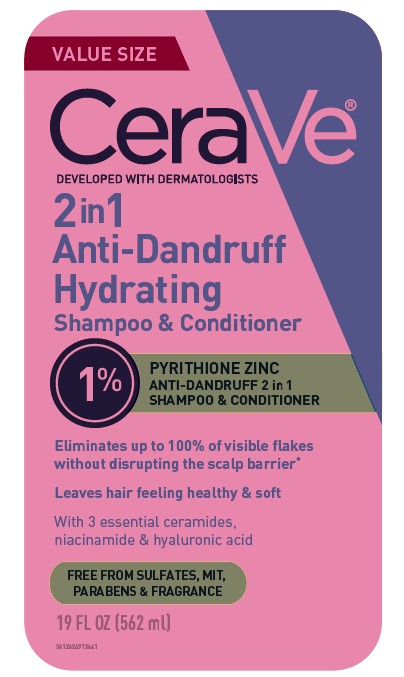 DRUG LABEL: CeraVe 2 in1 Anti Dandruff Hydrating Conditioner
NDC: 82046-266 | Form: SHAMPOO
Manufacturer: L'Oreal USA Products Inc
Category: otc | Type: HUMAN OTC DRUG LABEL
Date: 20251202

ACTIVE INGREDIENTS: PYRITHIONE ZINC 10 mg/1 mL
INACTIVE INGREDIENTS: WATER; SODIUM C14-16 OLEFIN SULFONATE; DISODIUM LAURETH SULFOSUCCINATE; DISODIUM COCOAMPHODIACETATE; SODIUM CHLORIDE; GLYCOL DISTEARATE; AMODIMETHICONE (1300 CST); SODIUM LAURYL SULFOACETATE; PPG-5-CETETH-20; COCAMIDE MIPA; SODIUM HYDROLYZED POTATO STARCH DODECENYLSUCCINATE; CERAMIDE NP; CERAMIDE AP; CARBOMER; NIACINAMIDE; TRIDECETH-6; TRIETHYL CITRATE; SODIUM HYDRIDE; SODIUM BENZOATE; SODIUM LAUROYL LACTYLATE; SALICYLIC ACID; SODIUM HYALURONATE; CHOLESTEROL; PHENOXYETHANOL; PROPYLENE GLYCOL; COCO-BETAINE; CITRIC ACID; TETRASODIUM GLUTAMATE DIACETATE; CETRIMONIUM CHLORIDE; CAPRYLYL GLYCOL; XANTHAN GUM; PHYTOSPHINGOSINE; POLYQUATERNIUM-10 (10000 MPA.S AT 2%); BENZOIC ACID

Drug Facts

Active ingredient

Pyrithione zinc 1%

Purpose

Anti-dandruff

Use

helps prevent recurrence of scalp flaking and itching associated with dandruff

Warnings

For external use only

When using this product

avoid contact with the eyes. If contact occurs, rinse eyes thoroughly with water.

Stop use and ask a doctor

If condition worsens or does not improve after regular use of this product as directed.

Keep out of reach of children

If swallowed, get medical help or contact a Poison Control Center right away

Directions

- for best results use at lease twice a week or as directed by a doctor
- wet hair and massage onto scalp
- rinse and repeat if desired

Inactive Ingredients

water, sodium C14-16 olefin sulfonate, disodium laureth sulfosuccinate, disodium cocoamphodiacetate,sodium chloride, glycol distearate, amodimethicone, sodium lauryl sulfoacetate, PPG-5-ceteth-20,cocamide MIPA, potato starch modified, ceramide NP, ceramide AP, ceramide EOP, carbomer, Niacinamide, trideceth-6, triethyl citrate, sodium hydroxide, sodium benzoate, sodium lauroyl lactylate, salicylic acid, sodium polynaphthalenesulfonate, sodium hyaluronate, cholesterol, phenoxyethanol, coco-betaine,propylene glycol, citric acid, tetrasodium glutamate diacetate, cetrimonium chloride, caprylyl glycol, xanthan gum, phytosphingosine, polyquaternium-10, acrylates copolymer, benzoic acid

Question or comments?

Toll-free number 1-888-768-2915